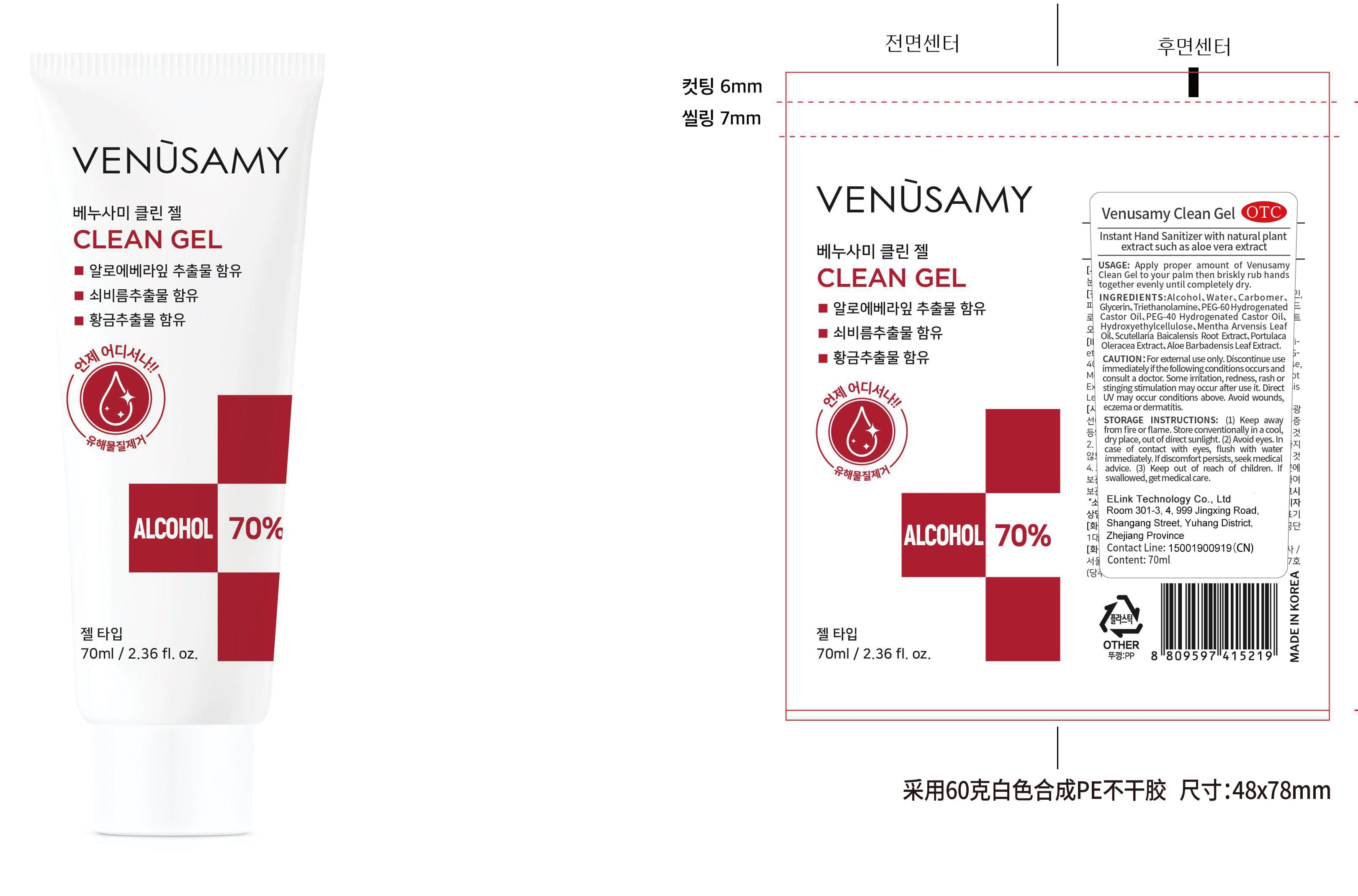 DRUG LABEL: Venusamy clean gel
NDC: 55418-001 | Form: GEL
Manufacturer: ELink Technology Co., Ltd.
Category: otc | Type: HUMAN OTC DRUG LABEL
Date: 20200423

ACTIVE INGREDIENTS: ALCOHOL 49 mL/70 mL
INACTIVE INGREDIENTS: POLYOXYL 40 HYDROGENATED CASTOR OIL; WATER; CARBOMER HOMOPOLYMER, UNSPECIFIED TYPE; PURSLANE; GLYCERIN; TROLAMINE; HYDROXYETHYL CELLULOSE, UNSPECIFIED; ALOE VERA LEAF; PEG-60 HYDROGENATED CASTOR OIL; MENTHA ARVENSIS LEAF OIL; SCUTELLARIA BAICALENSIS ROOT

DOSAGE AND ADMINISTRATION

Keep away from fire or flame. Store conventionallyin a cool,dry place, out of direct sunlight.

INACTIVE INGREDIENT

Water

Carbomer

Glycerin

Triethanolamine

PEG-60 Hydrogenated Castor Oil

PEG-40 Hydrogenated Castor Oil

Hydroxyethylcellulose

Mentha Arvensis Leaf Oil

Scutellaria Baicalensis Root Extract

Portulaca Oleracea Extract

Aloe Barbadensis Leaf Extract

INDICATIONS AND USAGE

Apply proper amount of Venusamy Clean Gel to your palm then briskly rub hands together evenly until completely dry.

ACTIVE INGREDIENT

Alcohol

keep out of children

PURPOSE

Disinfection
Sterilization
No Rinseing

WARNINGS

For etemal use only. Discontinue use immediatelyif the fllowing conditionsoccurs and consult a doctor. Some imitaton, redness, rash or
stinging stimulation may occur ater use it Direct UV may occur conditlons above. Avoid wounds,eczema or dermatitis.